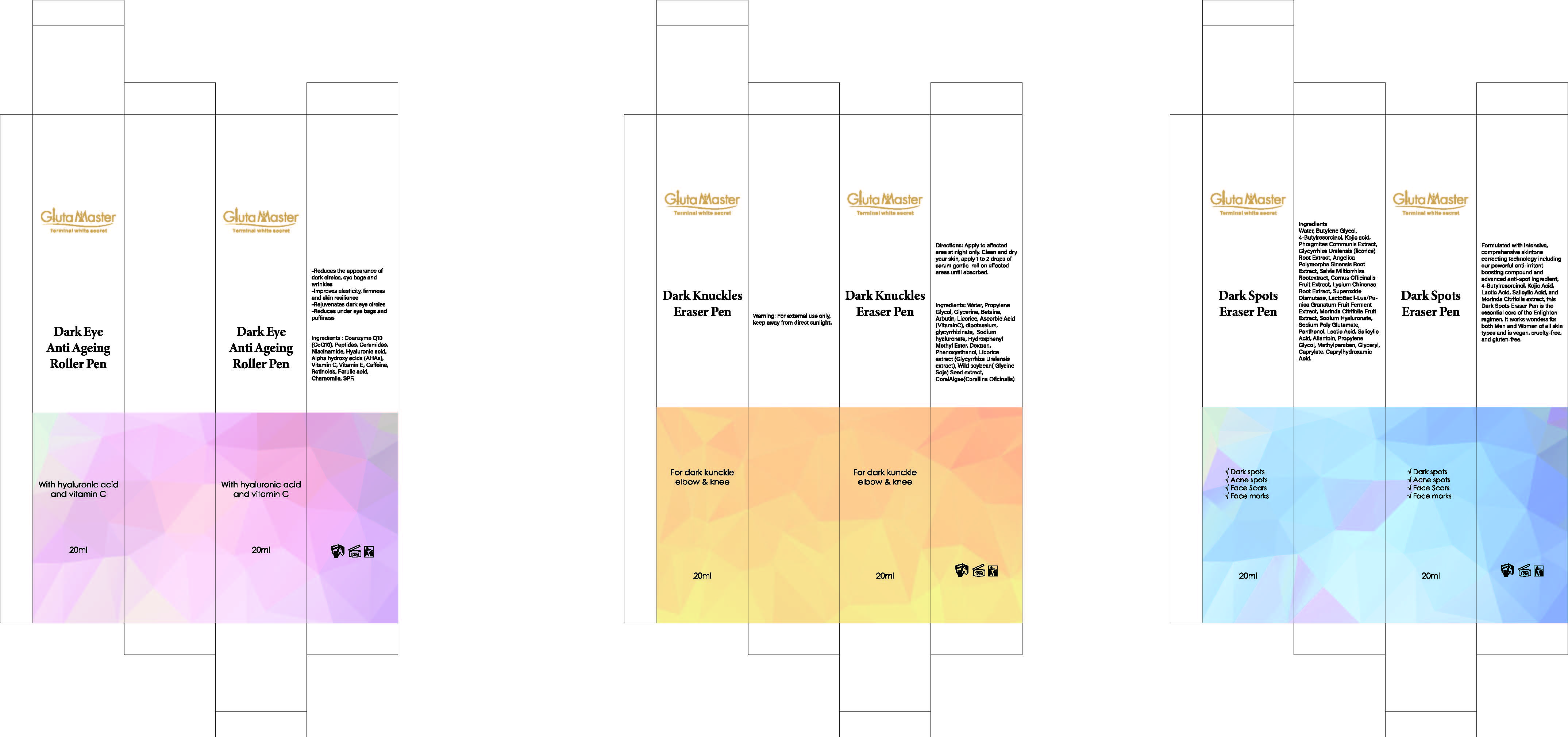 DRUG LABEL: dark spots eraser pen
NDC: 84423-087 | Form: SOLUTION, CONCENTRATE
Manufacturer: Guangzhou Kadiya Biotechnology Co., Ltd.
Category: otc | Type: HUMAN OTC DRUG LABEL
Date: 20250801

ACTIVE INGREDIENTS: SALICYLIC ACID 0.4 g/20 g; KOJIC ACID 0.24 g/20 g
INACTIVE INGREDIENTS: BUTYLENE GLYCOL; PHRAGMITES AUSTRALIS WHOLE; WATER; GLYCYRRHIZA URALENSIS ROOT; MORINDA CITRIFOLIA FRUIT; CORNUS OFFICINALIS FRUIT; SUPEROXIDE DISMUTASE; LACTIC ACID; METHYLPARABEN; GLYCERYL CAPRYLATE; ALLANTOIN; CAPRYLHYDROXAMIC ACID; SODIUM HYALURONATE; SODIUM POLYGLUTAMATE (200000 MW); PANTHENOL; PROPYLENE GLYCOL; 4-BUTYLRESORCINOL

PURPOSE

For whitening, Moisturizing, Antioxidant

INACTIVE INGREDIENT

Water
Butylene Glycol
4-Butylresorcinol
Phragmites Communis Extract
Glycyrrhiza Uralensis (licorice)Root Extract
Cornus OfficinalisFruit Extract
SuperoxideDismutase
Morinda Citrifolia FruitExtract
Sodium Hyaluronate
Sodium Poly Glutamate
Panthenol
Lactic Acid
Allantoin
PropyleneGlycol
Methylparaben
GlycerylCaprylate
CaprylhydroxamicAcid

Warning.

1、For external use only, avoid contact with eyes when used

2、Keep out of reach of children

INDICATIONS AND USAGE

Formulated with intensive, comprehensive skintone correcting technology including our powerful anti-irritant boosting compound and advanced anti-spot ingredient, 4-Butylresorcinol, Kojic Acid, Lactic Acid, Salicylic Acid, and Morinda Citrifolia extract, this Dark Spots Eraser Pen is the essential core of the Enlighten regimen, It works wonders for both Men and Women of all skin types and is vegan, cruelty-free, and gluten-free.

DOSAGE AND ADMINISTRATION

Formulated with intensive, comprehensive skintone correcting technology including our powerful anti-irritant boosting compound and advanced anti-spot ingredient, 4-Butylresorcinol, Kojic Acid, Lactic Acid, Salicylic Acid, and Morinda Citrifolia extract, this Dark Spots Eraser Pen is the essential core of the Enlighten regimen, It works wonders for both Men and Women of all skin types and is vegan, cruelty-free, and gluten-free.

KEEP OUT OF REACH OF CHILDREN SECTION

Active Ingredients
Kojic acid1.2%
SalicylicAcid2%

PACKAGE LABEL

Active Ingredients
Kojic acid1.2%
SalicylicAcid2%
Uses：
For whitening, Moisturizing, Antioxidant
The storage method：
Store sealed in a cool place and out of sunlight
Warning.
1、For external use only, avoid contact with eyes when used
2、Keep out of reach of children
Water
Butylene Glycol
4-Butylresorcinol
Phragmites Communis Extract
Glycyrrhiza Uralensis (licorice)Root Extract
Cornus OfficinalisFruit Extract
SuperoxideDismutase
Morinda Citrifolia FruitExtract
Sodium Hyaluronate
Sodium Poly Glutamate
Panthenol
Lactic Acid
Allantoin
PropyleneGlycol
Methylparaben
GlycerylCaprylate
CaprylhydroxamicAcid